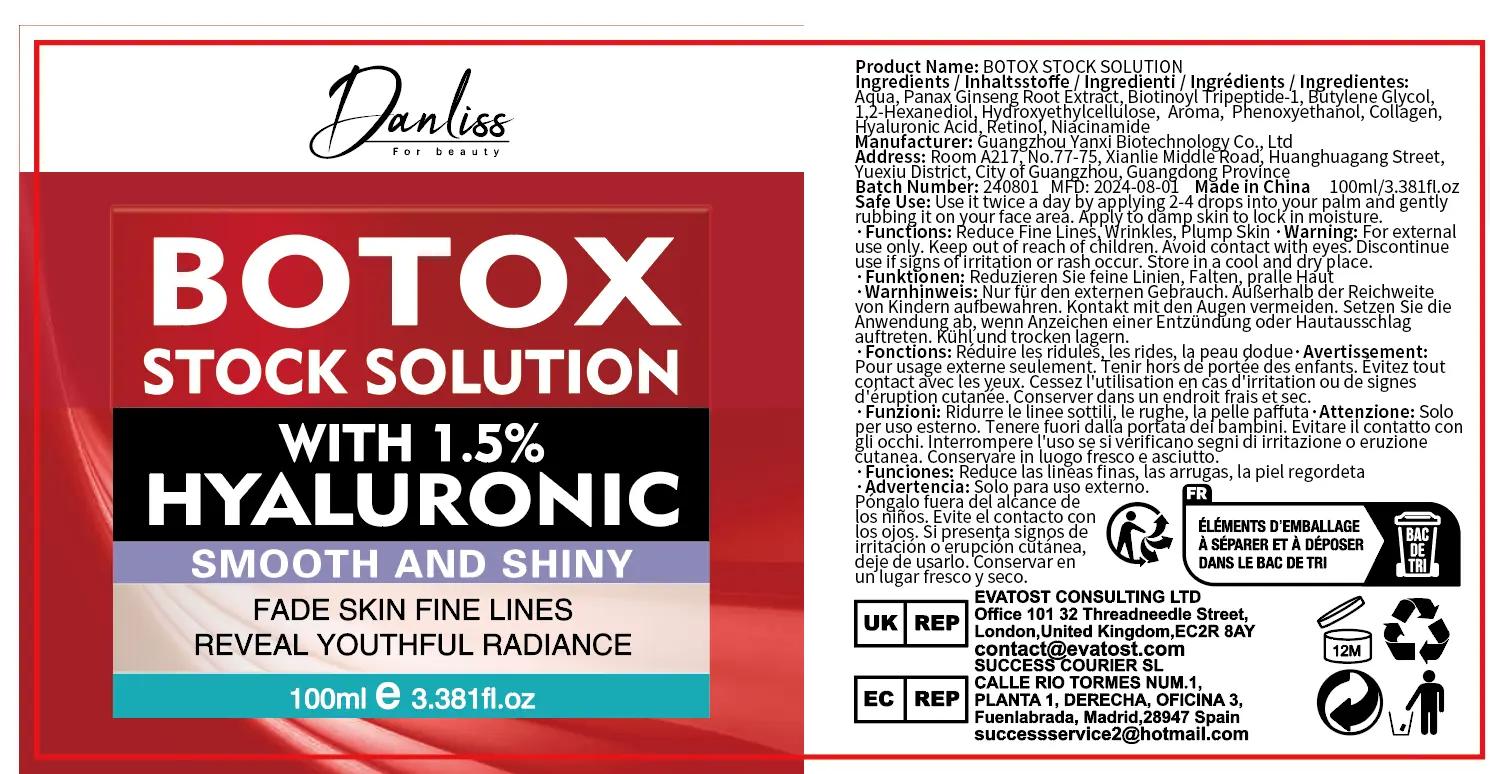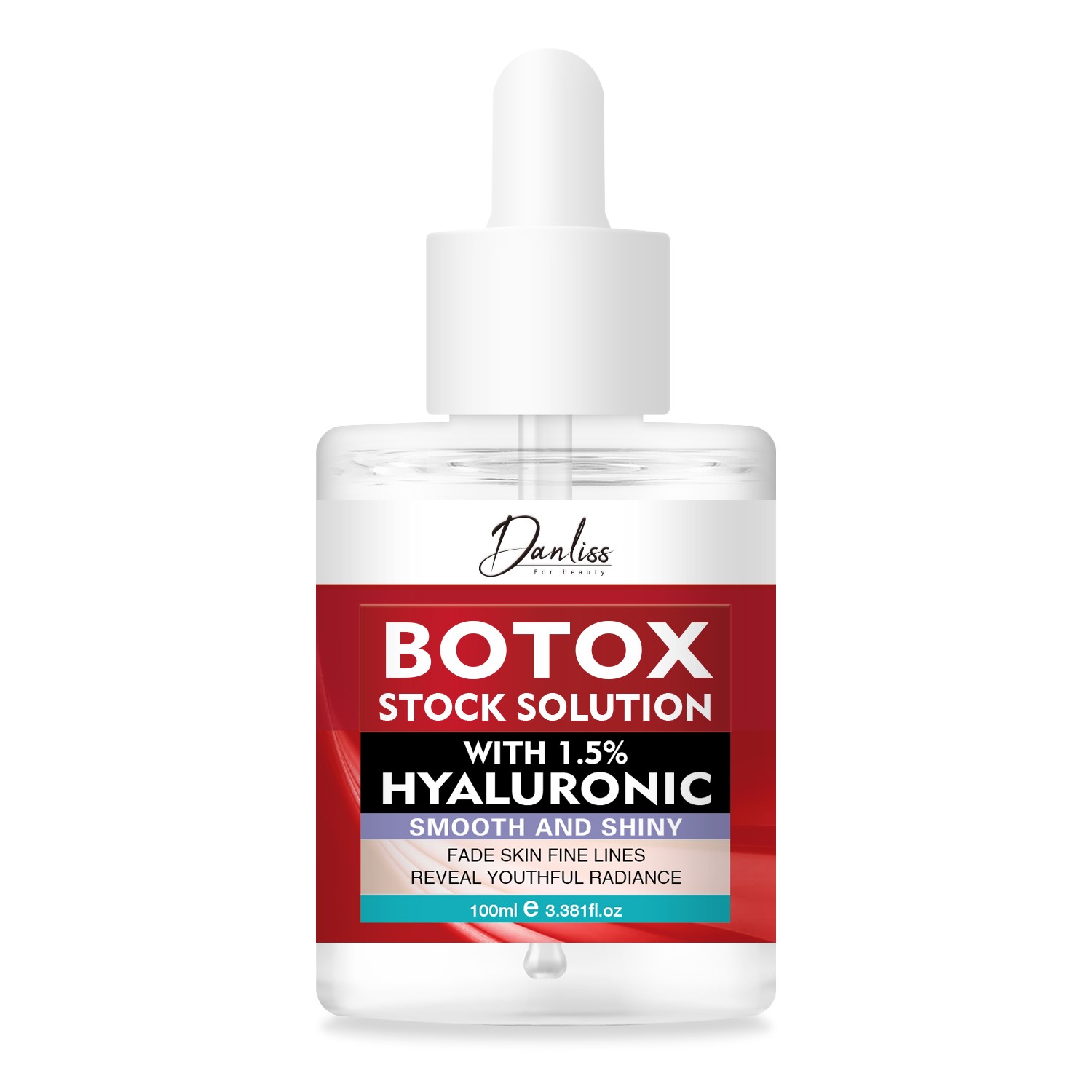 DRUG LABEL: Botox Stock Solution
NDC: 84025-242 | Form: LIQUID
Manufacturer: Guangzhou Yanxi Biotechnology Co., Ltd
Category: otc | Type: HUMAN OTC DRUG LABEL
Date: 20241103

ACTIVE INGREDIENTS: BUTYLENE GLYCOL 3 mg/100 mL; BIOTINOYL TRIPEPTIDE-1 5 mg/100 mL
INACTIVE INGREDIENTS: WATER

DOSAGE AND ADMINISTRATION

Use it twice a day by applying 2-4 drops into your palm and gently rubbing it on your face area. Apply to damp skin to lock in moisture.

WARNINGS

Keep out of children

INACTIVE INGREDIENT

Aqua

INDICATIONS AND USAGE

for daily face care

keep out of children

PURPOSE

Reduce Fine Lines, Wrinkles, Plump Skin